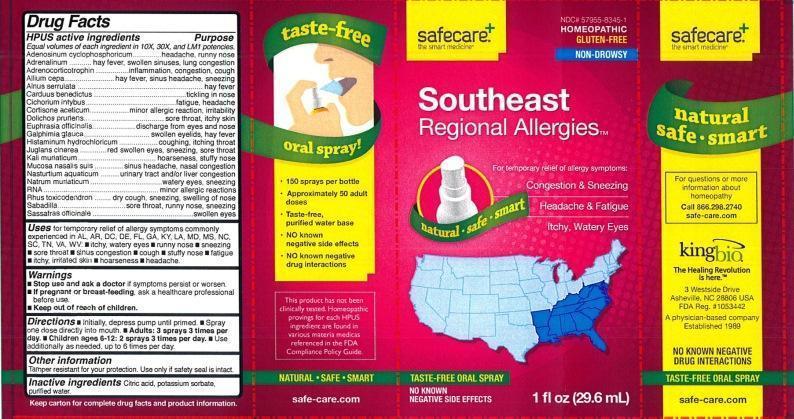 DRUG LABEL: Southeast Regional Allergies
NDC: 57955-8345 | Form: LIQUID
Manufacturer: King Bio Inc.
Category: homeopathic | Type: HUMAN OTC DRUG LABEL
Date: 20131104

ACTIVE INGREDIENTS: ADENOSINE CYCLIC PHOSPHATE 10 [hp_X]/29.6 mL; EPINEPHRINE 10 [hp_X]/29.6 mL; CORTICOTROPIN 10 [hp_X]/29.6 mL; ONION 10 [hp_X]/29.6 mL; ALNUS SERRULATA BARK 10 [hp_X]/29.6 mL; CENTAUREA BENEDICTA 10 [hp_X]/29.6 mL; CHICORY ROOT 10 [hp_X]/29.6 mL; CORTISONE ACETATE 10 [hp_X]/29.6 mL; MUCUNA PRURIENS FRUIT TRICHOME 10 [hp_X]/29.6 mL; EUPHRASIA STRICTA 10 [hp_X]/29.6 mL; GALPHIMIA GLAUCA FLOWERING TOP 10 [hp_X]/29.6 mL; HISTAMINE DIHYDROCHLORIDE 10 [hp_X]/29.6 mL; JUGLANS CINEREA BRANCH BARK/ROOT BARK 10 [hp_X]/29.6 mL; POTASSIUM CHLORIDE 10 [hp_X]/29.6 mL; SUS SCROFA NASAL MUCOSA 10 [hp_X]/29.6 mL; NASTURTIUM OFFICINALE 10 [hp_X]/29.6 mL; SODIUM CHLORIDE 10 [hp_X]/29.6 mL; SACCHAROMYCES CEREVISIAE RNA 10 [hp_X]/29.6 mL; TOXICODENDRON PUBESCENS LEAF 10 [hp_X]/29.6 mL; SCHOENOCAULON OFFICINALE SEED 10 [hp_X]/29.6 mL; SASSAFRAS ALBIDUM ROOT BARK 10 [hp_X]/29.6 mL
INACTIVE INGREDIENTS: CITRIC ACID MONOHYDRATE; POTASSIUM SORBATE; WATER

Southeast Regional Allergies™

Drug Facts

____________________________________________________________________________________________________________

Equal volumes of each ingredient in 10X, 30X, and LM1 potencies.

HPUS active ingredients: Adenosinum cyclophosphoricum, Adrenalinum, Adrenocorticotrophin, Allium cepa, Alnus serrulata, Carduus benedictus, Cichorium intybus, Cortisone aceticum, Dolichos pruriens, Euphrasia officinalis, Galphimia glauca, Histaminum hydrochloricum, Juglans cinerea, Kali muriaticum, Mucosa nasalis suis, Nasturtium aquaticum, Natrum muriaticum, RNA, Rhus toxicodendron, Sabadilla, Sassafras officinale.

INDICATIONS AND USAGE

Uses for temporary relief of allergy symptoms commonly experienced in AL, AR, DC, DE, FL, GA, KY, LA, MD, MS, NC, SC, TN, VA, WV:

- itchy, watery eyes
- runny nose
- sneezing
- sore throat
- sinus congestion
- cough
- stuffy nose
- fatigue
- itchy, irritated skin
- hoarseness
- headache

Warnings

- Stop use and ask a doctor if symptoms persist or worsen.
- If pregnant or breast-feeding, ask a healthcare professional before use.

- Keep out of reach of children.

Directions:

- Initially, depress pump until primed.
- Spray one dose directly into mouth.
- Adults: 3 sprays 3 times per day.
- Children ages 6-12: 2 sprays 3 times per day.
- Use additionally as needed, up to 6 times per day.

OTHER SAFETY INFORMATION

Tamper resistant for your protection. Use only if safety seal is intact.

Inactive Ingredients: Citric acid, potassium sorbate, purified water.

Drug Facts

__________________________________________________________________________________________________________________

HPUS active ingredients Purpose

Equal volumes of each ingredient in 10X, 30X, and LM1 potencies.

Adenosinum cyclophosphoricum............................................headache, runny nose

Adrenalinum.......................................................................hay fever, swollen sinuses, lung congestion

Adrenocorticotrophin............................................................inflammation, congestion, cough

Allium cepa.........................................................................hay fever, sinus headache, sneezing

Alnus serrulata...................................................................hay fever

Carduus benedictus.............................................................tickling in nose

Cichorium intybus................................................................fatigue, headache

Cortisone aceticum..............................................................minor allergic reaction, irritability

Dolichos pruriens..................................................................sore throat, itchy skin

Euphrasia officinalis.............................................................discharge from eyes and nose

Galphimia glauca.................................................................swollen eyelids, hay fever

Histaminum hydrochloricum..................................................coughing, itching throat

Juglans cinerea....................................................................red swollen eyes, sneezing, sore throat

Kali muriaticum...................................................................hoarseness, stuffy nose

Mucosa nasalis suis..............................................................sinus headache, nasal congestion

Nasturtium aquaticum..........................................................urinary tract and or liver congestion

Natrum muriaticum..............................................................watery eyes, sneezing

RNA...................................................................................minor allergic reactions

Rhus toxicodendron..............................................................dry cough, sneezing, swelling of nose

Sabadilla.............................................................................sore throat, runny nose, sneezing

Sassafras officinale...............................................................swollen eyes